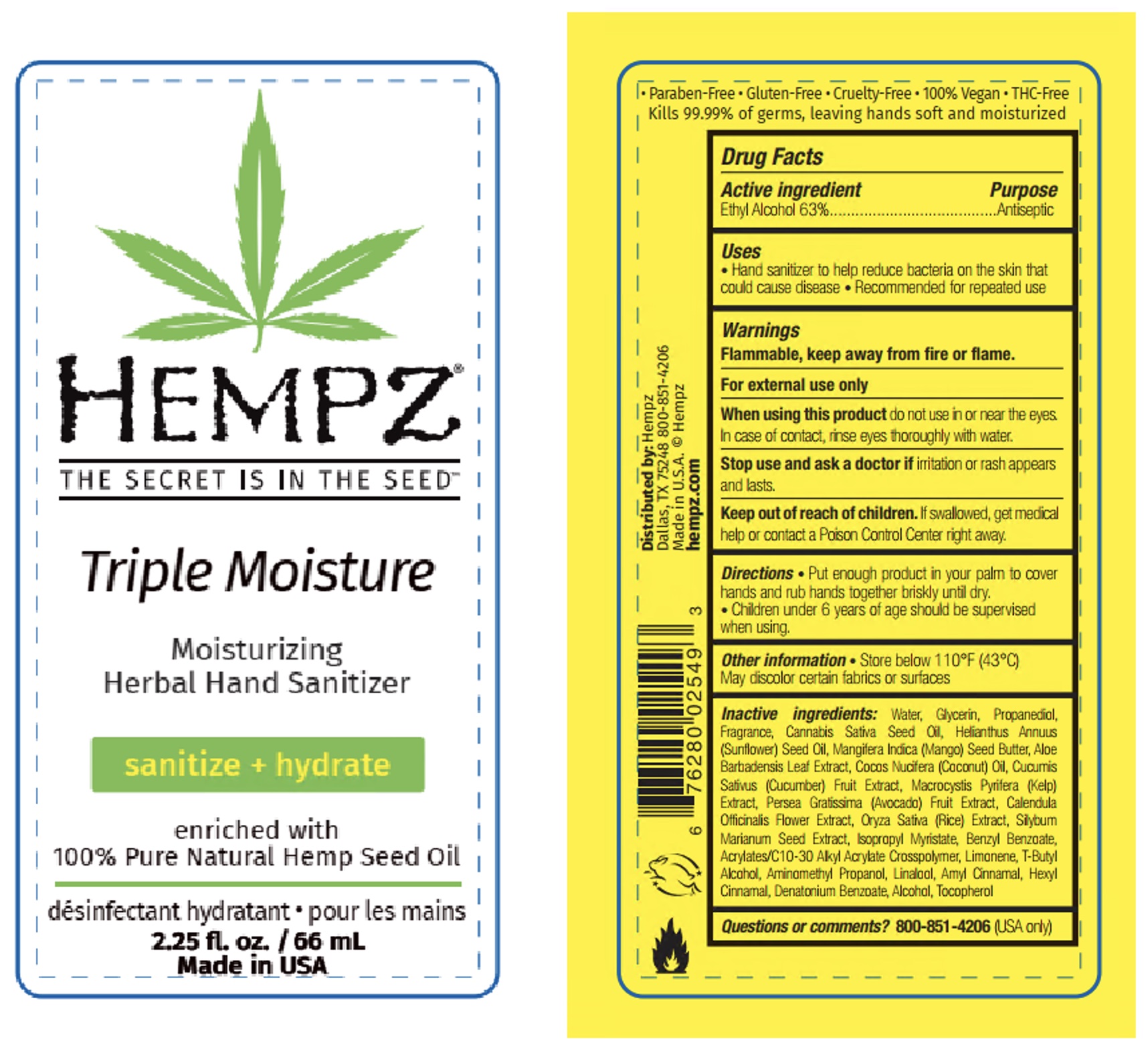 DRUG LABEL: Hempz Triple Moisture Moisturizing Herbal Hand Sanitizer
NDC: 84853-0001 | Form: GEL
Manufacturer: PBIGROUP, LLC
Category: otc | Type: HUMAN OTC DRUG LABEL
Date: 20241024

ACTIVE INGREDIENTS: ALCOHOL 41.58 g/66 mL
INACTIVE INGREDIENTS: WATER; GLYCERIN; PROPANEDIOL; CANNABIS SATIVA SEED OIL; SUNFLOWER OIL; MANGIFERA INDICA SEED BUTTER; ALOE VERA LEAF; COCONUT OIL; CUCUMBER; MACROCYSTIS PYRIFERA; AVOCADO; CALENDULA OFFICINALIS FLOWER; RICE GERM; SILYBUM MARIANUM SEED; ISOPROPYL MYRISTATE; BENZYL BENZOATE; LIMONENE, (+)-; TERT-BUTYL ALCOHOL; AMINOMETHYLPROPANOL; LINALOOL, (+/-)-; .ALPHA.-AMYLCINNAMALDEHYDE; .ALPHA.-HEXYLCINNAMALDEHYDE; DENATONIUM BENZOATE; TOCOPHEROL

HEMPZ TRIPLE MOISTURE MOISTURIZING HERBAL HAND SANTIZER

Active ingredient

Alcohol 63%

Purpose

Antiseptic

Uses

- Hand sanitizer to help reduce bacteria on the skin that could cause disease.
- Recommended for repeated use

Warnings

Flammable, keep away from fire or flame.

For external use only.

When using this product

Do not use in or near the eyes. In case of contact, rinse eyes thoroughly with water.

Stop use and ask a doctor if

Irritation or rash appears or lasts.

Keep out of reach of children

If swallowed, get medical help or contact a Poison Control Center right away.

Directions

•Put enough product in your palm to cover hands and rub hands together briskly until dry.

•Children under 6 years of age should be supervised when using.

Other information

•Store below 110°F (43°C). May discolor certain fabrics or surfaces.

Inactive ingredients

Water, Glycerin, Propanediol, Fragrance, Cannabis Sativa Seed Oil, Helianthus Annuus (Sunflower) Seed Oil, Mangifera Indica (Mango) Seed Butter, Aloe Barbadensis Leaf Extract, Cocos Nucifera (Coconut) Oil, Cucumis Sativus (Cucumber) Fruit Extract, Macrocystis Pyrifera (Kelp) Extract, Persea Gratissima (Avocado) Fruit Extract, Calendula Officinalis Flower Extract, Oryza Sativa (Rice) Extract, Silybum Marianum Seed Extract, Isopropyl Myristate, Benzyl Benzoate, Acrylates/C10-30 Alkyl Acrylate Crosspolymer, Limonene, T-Butyl Alcohol, Aminomethyl Propanol, Linalool, Amyl Cinnamal, Hexyl Cinnamal, Denatonium Benzoate, Alcohol, Tocopherol

Questions or comments?

800-851-4206 (USA only)

SPL Unclassified

• Paraben-Free • Gluten-Free • Cruelty-Free • 100% Vegan • THC-Free
Kills 99.99% of germs, leaving hands soft and moisturized

Distributed by: Hempz
Dallas, TX 75248 800-851-4206
Made in U.S.A. © Hempz